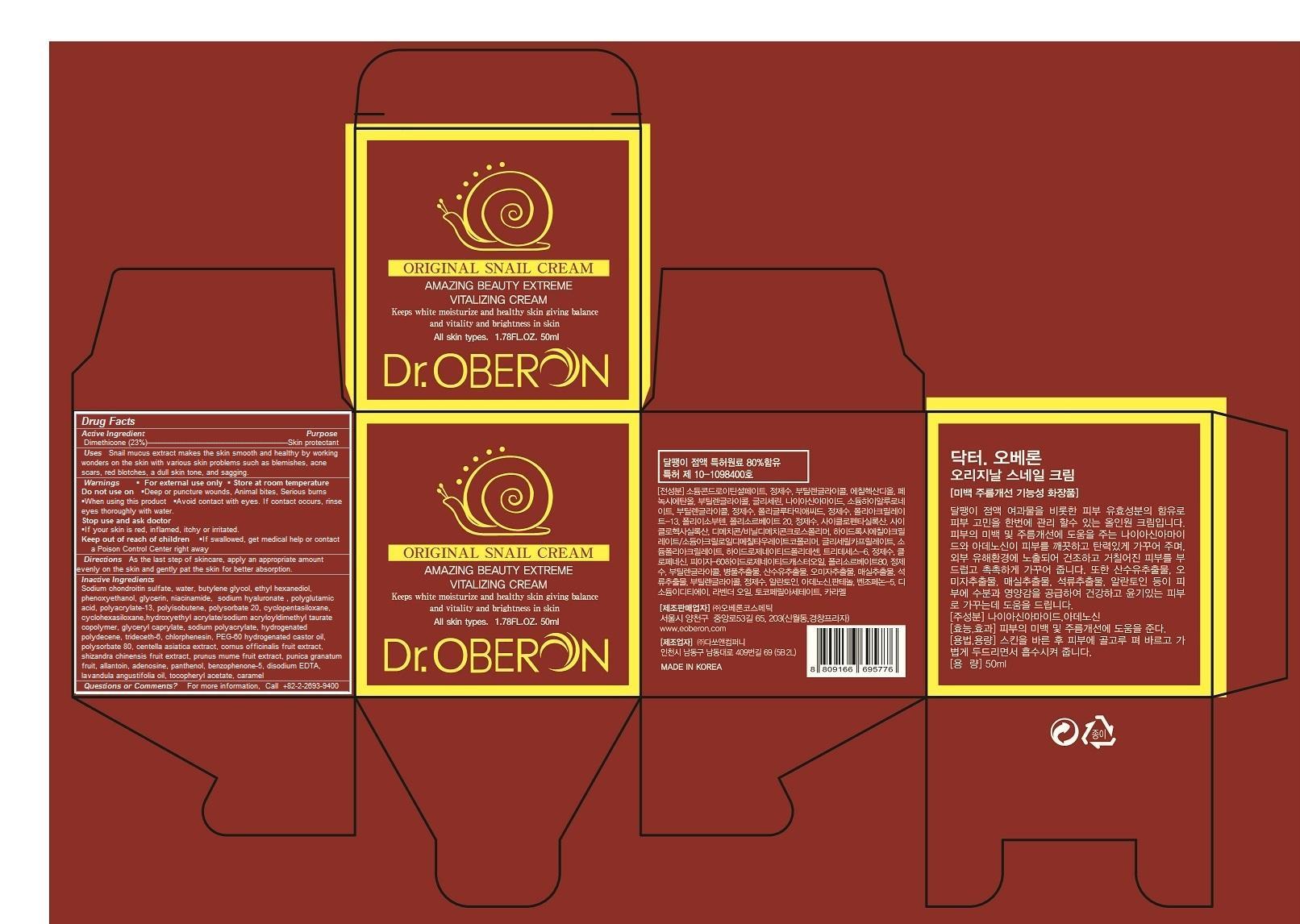 DRUG LABEL: Dr. Oberon Original Snail Cream
NDC: 52891-105 | Form: CREAM
Manufacturer: Oberon Cosmetic Co., Ltd.
Category: otc | Type: HUMAN OTC DRUG LABEL
Date: 20140626

ACTIVE INGREDIENTS: DIMETHICONE 11.5 g/50 g
INACTIVE INGREDIENTS: SODIUM CHONDROITIN SULFATE (PORCINE; 5500 MW); water; BUTYLENE GLYCOL; ETHOHEXADIOL; PHENOXYETHANOL; glycerin; niacinamide; HYALURONATE SODIUM; POLYISOBUTYLENE (1000 MW); POLYSORBATE 20; CYCLOMETHICONE 5; CYCLOMETHICONE 6; HYDROXYETHYL ACRYLATE/SODIUM ACRYLOYLDIMETHYL TAURATE COPOLYMER (45000 MPA.S AT 1%); GLYCERYL CAPRYLATE; SODIUM POLYACRYLATE (8000 MW); HYDROGENATED POLYDECENE (550 MW); TRIDECETH-6; chlorphenesin; PEG-60 HYDROGENATED CASTOR OIL; POLYSORBATE 80; CENTELLA ASIATICA; CORNUS OFFICINALIS FRUIT; PRUNUS MUME FRUIT; PUNICA GRANATUM WHOLE; allantoin; adenosine; panthenol; BENZOPHENONE-5; DISODIUM EDTA-COPPER; LAVANDULA ANGUSTIFOLIA WHOLE; .ALPHA.-TOCOPHEROL ACETATE; caramel

Dr. Oberon Original Snail Cream